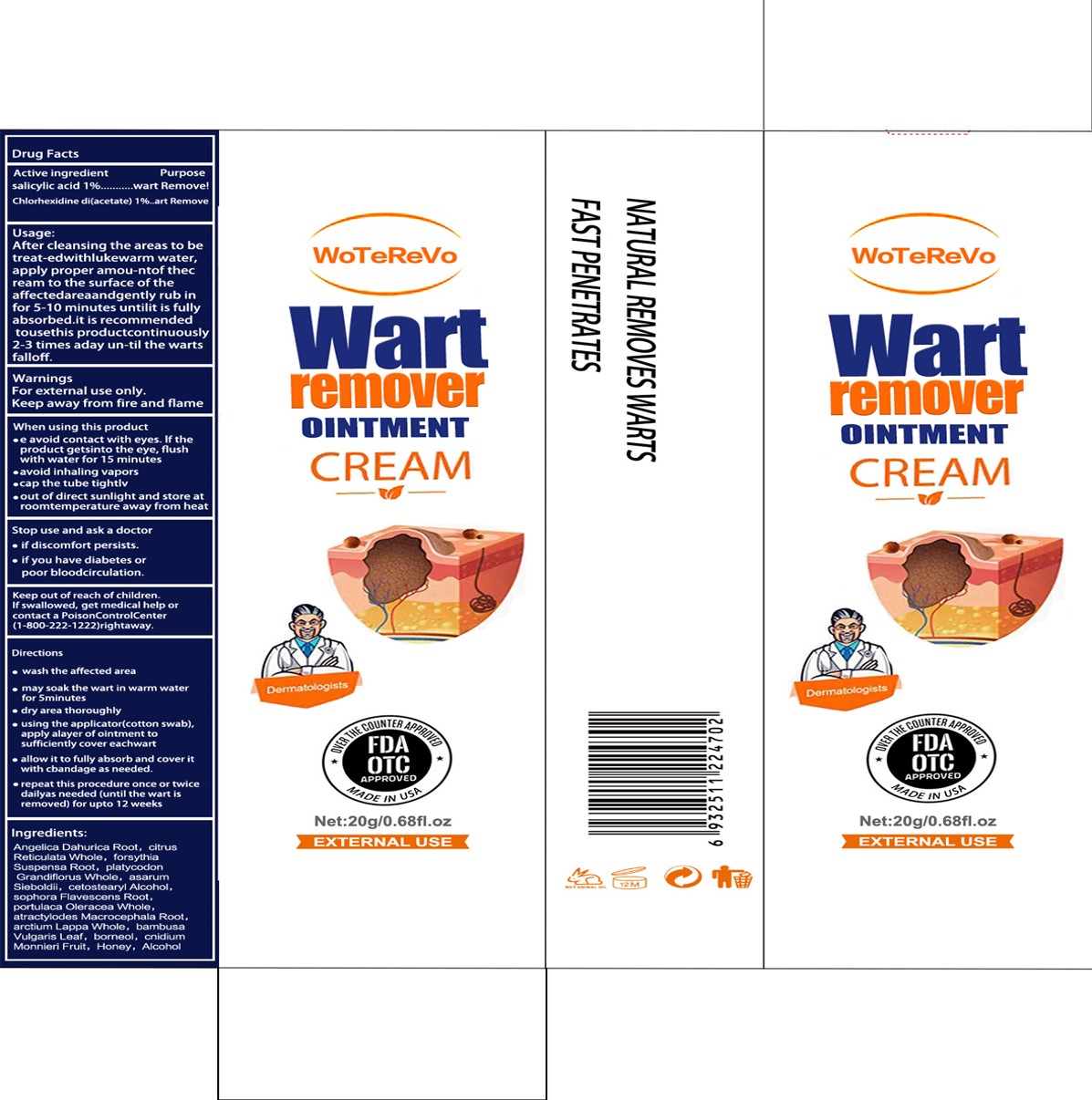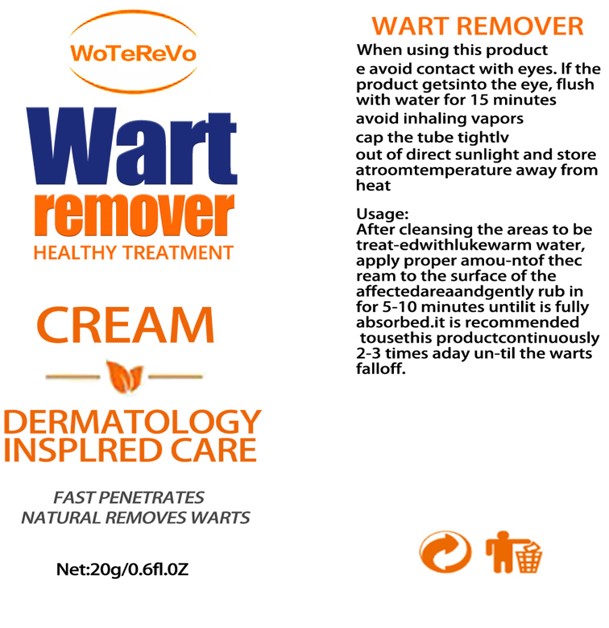 DRUG LABEL: Wart Remover
NDC: 84288-005 | Form: OINTMENT
Manufacturer: Dongkou County Hecheng Network Technology Co., Ltd.
Category: otc | Type: HUMAN OTC DRUG LABEL
Date: 20240802

ACTIVE INGREDIENTS: SALICYLIC ACID 1 g/100 g; CHLORHEXIDINE 1 g/100 g
INACTIVE INGREDIENTS: ATRACTYLODES MACROCEPHALA ROOT; ARCTIUM LAPPA WHOLE; CITRUS RETICULATA WHOLE; ASARUM SIEBOLDII; SOPHORA FLAVESCENS ROOT; BAMBUSA VULGARIS LEAF; HONEY; CNIDIUM MONNIERI FRUIT; PLATYCODON GRANDIFLORUS WHOLE; CETOSTEARYL ALCOHOL; FORSYTHIA SUSPENSA ROOT; BORNEOL; PORTULACA OLERACEA WHOLE; ALCOHOL; ANGELICA DAHURICA ROOT

Wart Remover

ACTIVE INGREDIENT

SALICYLIC ACID 1%
CHLORHEXIDINE 1%

PURPOSE

wart Remove

KEEP OUT OF REACH OF CHILDREN

Keep out of reach of childrenIfswallowed, get medical help orcontacta Poisoncontrolcenter(1-800-222-1222)rightaway

INDICATIONS AND USAGE

After cleansing the areas to betreat-edwithlukewarm water,apply proper amou-ntofthecream to the surface of theaffectedareaandgentlyrub infor 5-10 minutes untilit is fullyabsorbed.itisrecommendedtousethis productcontinuously2-3 times aday un-til the wartsfalloff.

WARNINGS

For external use only.
Keep away from fire and flame

DOSAGE AND ADMINISTRATION

wash the affected area
may soak the wart in warm water for 5minutes
dry area thoroughly
using the applicator(cotton swab),apply alayer of ointment to sufficiently cover eachwart
allow it to fully absorb and cover it with cbandage as needed.
repeat this procedure once ortwicedailyas needed (until the wart isremoved) for upto 12 weeks

STORAGE AND HANDLING

Store in a dry and cool place

INACTIVE INGREDIENT

ANGELICA DAHURICA ROOT
CITRUS RETICULATA WHOLE
FORSYTHIA SUSPENSA ROOT
PLATYCODON GRANDIFLORUS WHOLE
ASARUM SIEBOLDII
CETOSTEARYL ALCOHOL
SOPHORA FLAVESCENS ROOT
PORTULACA OLERACEA WHOLE
ATRACTYLODES MACROCEPHALA ROOT
ARCTIUM LAPPA WHOLE
BAMBUSA VULGARIS LEAF
BORNEOL
CNIDIUM MONNIERI FRUIT
HONEY
ALCOHOL